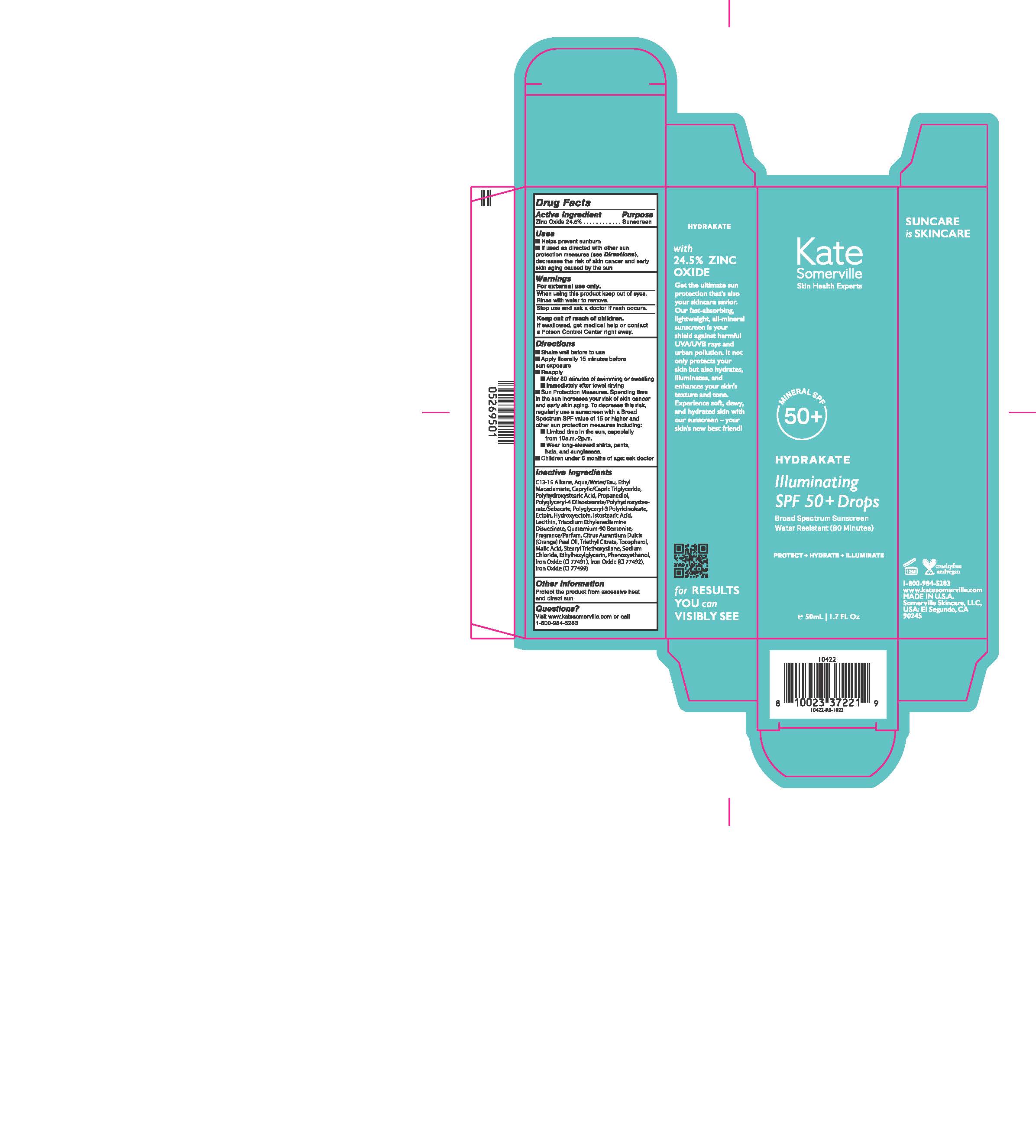 DRUG LABEL: Illuminating SPF 50 plus drops Broad Spectrum Sunscreen
NDC: 56152-0253 | Form: LOTION
Manufacturer: Cosmetic Enterprise Ltd
Category: otc | Type: HUMAN OTC DRUG LABEL
Date: 20251010

ACTIVE INGREDIENTS: ZINC OXIDE 24.5 g/100 mL
INACTIVE INGREDIENTS: MEDIUM-CHAIN TRIGLYCERIDES; ETHYLHEXYLGLYCERIN; PHENOXYETHANOL; ECTOINE; POLYHYDROXYSTEARIC ACID (2300 MW); TOCOPHEROL; FERRIC OXIDE YELLOW; ISOSTEARIC ACID; ETHYL MACADAMIATE; FERROSOFERRIC OXIDE; FERRIC OXIDE RED; SODIUM CHLORIDE; QUATERNIUM-90 BENTONITE; STEARYL TRIETHOXYSILANE; C13-15 ALKANE; WATER; PROPANEDIOL; POLYGLYCERYL-3 PENTARICINOLEATE; HYDROXYECTOIN; MALIC ACID; POLYGLYCERYL-4 DIISOSTEARATE/POLYHYDROXYSTEARATE/SEBACATE; ORANGE OIL, COLD PRESSED; LECITHIN, SOYBEAN; TRISODIUM ETHYLENEDIAMINE DISUCCINATE; TRIETHYL CITRATE

Illuminating SPF 50 plus drops Broad Spectrum Sunscreen

Active Ingredient Purpose

Zinc Oxide........ ....Sunscreen

Uses

- Helps prevent sunburn
- If used as directed with other sun protection measures (see Directions), decreases the risk of skin cancer and early skin aging caused by the sun

Keep out of reach of children.

If swallowed, get medical help or contact a Poison Control Center right away.

Stop use and ask a doctor is rash occurs

Warnings

For external use only

When using this product keep out of eyes, rinse with water to remove.

Directions

- Shake well before use
- Apply liberally 15 minutes before sun exposure
- Reapply
- After 80 minutes of swimming or sweating
- immediately after towel drying
- Sun Protection Meaures. Spending time under the sun increases your risk of skin cancer and early skin aging. To decrease the risk, regurlarly use a sunscreen with an SPF of 15 or higher, and other sun protection meaures, including:
- limit time under the sun, especially from 10:00 a.m. to 2:00 p.m.
- wear long-sleeve shirts, pants, hats, and sunglasses
- children under 6 months of age: ask doctor

Inactive Ingredients

C13-15 Alkane, Aqua/water/Eau, Ethyl Macadamiate, Caprylic/Capric Triglyceride, Polyhydroxystearic Acid, Propanediol, Polyglyceryl-4 Diisostearate/Polyhydroxystearate/Sebacate, Polyglyceryl-3 Polyricinoleate, Ectoin, Hydroxyectoin, Isostearic acid, Lecithin, Trisodium Ethylenediamine Disuccinate, Quaternium-90 Bentonite, Fragrance/Parfum, Citrus Aurantium Dulcis (Orange) Peel Oil, Triethyl Citrate, Tocopherol, Malic Acid, Stearyl Triethoxysilane, Sodium Chloride, Ethylhexylglycerin, Phenoxyethanol, Iron Oxide (CI 77491), Iron Oxide (CI 77492), Iron Oxide (CI 77499)

Other Information

Protect the product from excessive heat and direct sun

PACKAGE LABEL

Kate Somerville

Mineral SPF 50+

Hydrakate

Illuminating SPF 50+ Drops

Broad Spectrum Sunscreen

Water Resistant (80 Minutes)

50 mL 1.7 Fl. Oz